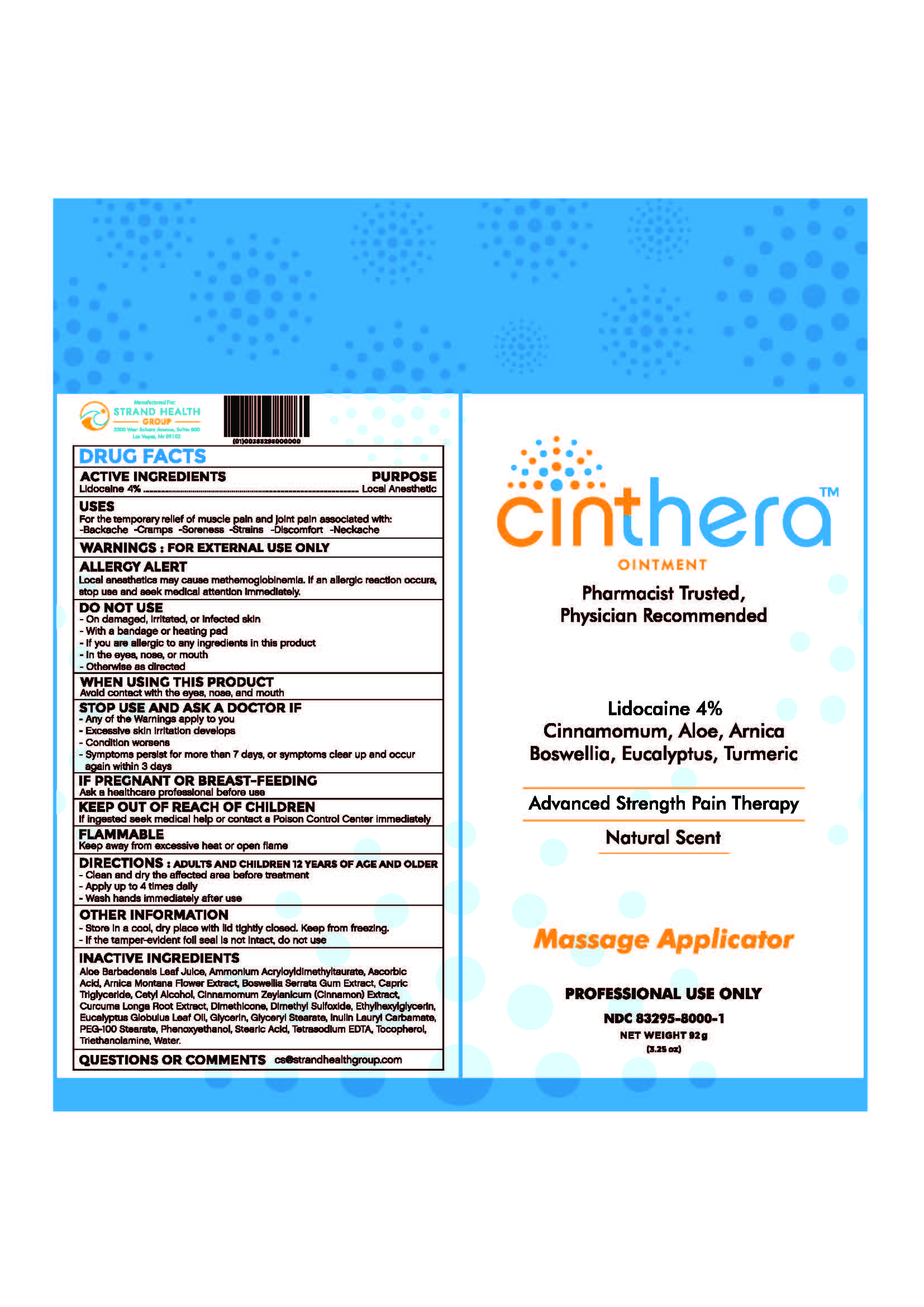 DRUG LABEL: Cinthera
NDC: 83295-8000 | Form: OINTMENT
Manufacturer: Strand Health Group
Category: otc | Type: HUMAN OTC DRUG LABEL
Date: 20251211

ACTIVE INGREDIENTS: LIDOCAINE 0.04 g/1 g
INACTIVE INGREDIENTS: CURCUMA LONGA (TURMERIC) ROOT; TRIETHANOLAMINE; TOCOPHEROL; TETRASODIUM EDTA; CINNAMON; PEG-100 STEARATE; WATER; AMMONIUM ACRYLOYLDIMETHYLTAURATE; TRICAPRIN; GLYCERYL STEARATE; ASCORBIC ACID; INULIN LAURYL CARBAMATE; ARNICA MONTANA FLOWER; DIMETHICONE; ETHYLHEXYLGLYCERIN; EUCALYPTUS GLOBULUS LEAF OIL; BOSWELLIA SERRATA GUM; CETYL ALCOHOL; GLYCERIN; ALOE VERA LEAF; DIMETHYL SULFOXIDE; STEARIC ACID; PHENOXYETHANOL

Cinthera Ointment

ACTIVE INGREDIENTS

Lidocaine 4%

PURPOSE

Local Anesthetic

USES

For the temporary relief of muscle pain and joint pain associated with:

-Backache -Cramps -Soreness -Strains -Discomfort -Neckache

ALLERGY ALERT

Local anesthetics may cause methemoglobinemia. If an allergic reaction occurs, stop use and seek medical attention immediately.

DO NOT USE

-On damaged, irritated, or infected skin

-With a bandage or heating pad

-If you are allergic to any ingredients in this product

-In the eyes, nose, or mouth

-Otherwise as directed

WHEN USING THIS PRODUCT

Avoid contact with the eyes, nose, and mouth

STOP USE AND ASK DOCTOR IF

-Any of the warnings apply to you

-Excessive skin irritation develops

-Condition worsens

-Symptoms persist for more than 7 days, or symptoms clear up and occur again within 3 days

IF PREGNANT OR BREASTFEEDING

Ask a healthcare professional before use

KEEP OUT OF REACH OF CHILDREN

If ingested, seek medical help or contact Poison Control immediately

FLAMMABLE

Keep away from excessive heat or open flame

DIRECTIONS

Adults and Children 12 Years of Age and Older:

-Clean and dry the affected area

-Apply up to 4 times daily

-Wash hands immediately after use

OTHER INFORMATION

-Store in a cool, dry place with lid tightly closed. Keep from freezing.

-If the tamper-evident foil seal is not intact, do not use

INACTIVE INGREDIENTS

Aloe Barbedensis Leaf Juice, Ammonium Acryloyldimethyltaurate, Ascorbic Acid, Arnica Montana Flower Extract, Boswellia Serrata Gum Extract, Capric Triglyceride, Cetyl Alcohol, Cinnamomum Zeylanicum (Cinnamon) Extract, Curcuma Longa Root Extract, Dimethicone, Dimethyl Sulfoxide, Ethylhexylglycerin, Eucalyptus Globulus Leaf Oil, Glycerin, Glyceryl Stearate, Inulin Lauryl Carbamate, PEG-100 Stearate, Phenoxyethanol, Steric Acid, Tetrasodium EDTA, Tocopherol, Triethanolamine, Water.

QUESTIONS OR COMMENTS

cs@strandhealthgroup.com